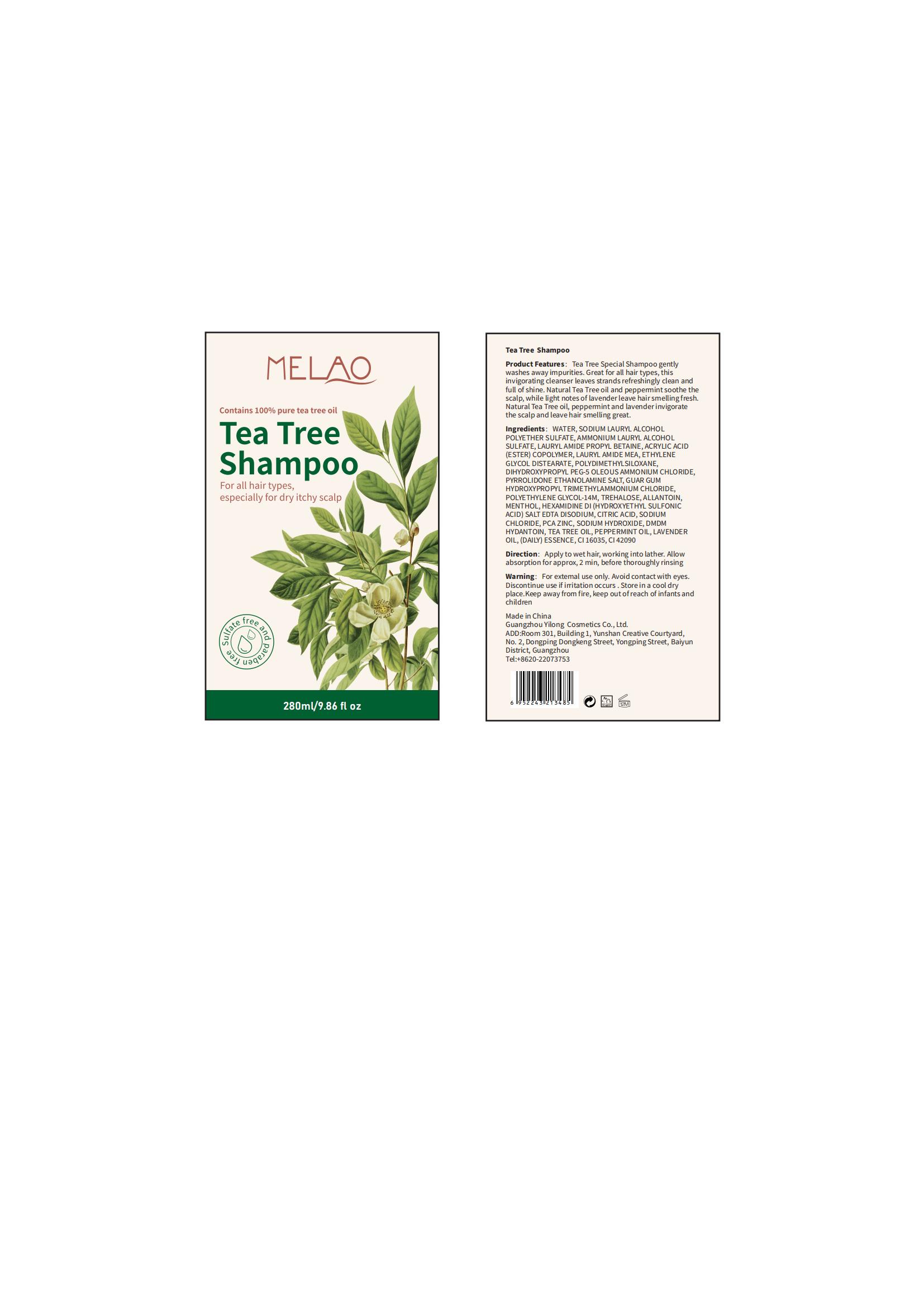 DRUG LABEL: MELAO Tea TreeShampoo
NDC: 83566-141 | Form: LIQUID
Manufacturer: Guangdong Aimu Biological Technology Co., Ltd
Category: otc | Type: HUMAN OTC DRUG LABEL
Date: 20240625

ACTIVE INGREDIENTS: PYRROLIDONE 0.3 g/100 mL
INACTIVE INGREDIENTS: SODIUM LAURYL GLYCOL CARBOXYLATE; TEA TREE OIL; SODIUM CHLORIDE; ALLANTOIN

MELAO Tea Tree Shampoo

Active ingredients

PYRROLIDONE ETHANOLAMINE SALT 0.3%

Purpose

Tea Tree Special Shampoo gently washes away impurities.

Uses

Apply to wet hair, working into lather. Allow absorption for approx, 2 min, before thoroughly rinsing.

Warnings

For external use only.

Stop use and ask a doctor if

rash occurs.

Do not use

on damaged or broken skin.

When using this product

keep out of eyes. Rinse with water to remove.

Keep out of reach of children.

If swallowed, get medical help or contact a Poison Control Center right away.

Dosage

Squeeze out an appropriate amount of product and spread evenly on wet hair.

Inactive ingredients

WATER 73.198%
SODIUM LAURYL ALCOHOL POLYETHER SULFATE 2%
AMMONIUM LAURYL ALCOHOL SULFATE 1%
LAURYLAMIDE PROPYL BETAINE 2%
ACRYLIC ACID (ESTER) COPOLYMER 1%
LAURYL AMIDE MEA 2%
ETHYLENE GLYCOL DISTEARATE 1%
POLYDIMETHYLSILOXANE 0.2%
DIHYDROXYPROPYL PEG-5 OLEOUS AMMONIUM CHLORIDE 0.5%
GUAR GUM HYDROXYPROPYL TRIMETHYLAMMONIUM CHLORIDE 2%
POLYETHYLENE GLYCOL-14M 0.3%
TREHALOSE 2%
ALLANTOIN 2%
MENTHOL 0.2%
HEXAMIDINE DI(HYDROXYETHYL SULFONIC ACID) SALT EDTA DISODIUM 0.2%
CITRIC ACID 2%
SODIUM CHLORIDE 0.2%
PCA ZINC 1%
SODIUM HYDROXIDE 0.3%
DMDM HYDANTOIN 0.5%
TEA TREE OIL 2%
PEPPERMINT OIL 2%
LAVENDER OIL 2%
(DAILY)ESSENCE 0.1%

CI 16035 0.001%
CI 42090 0.001%